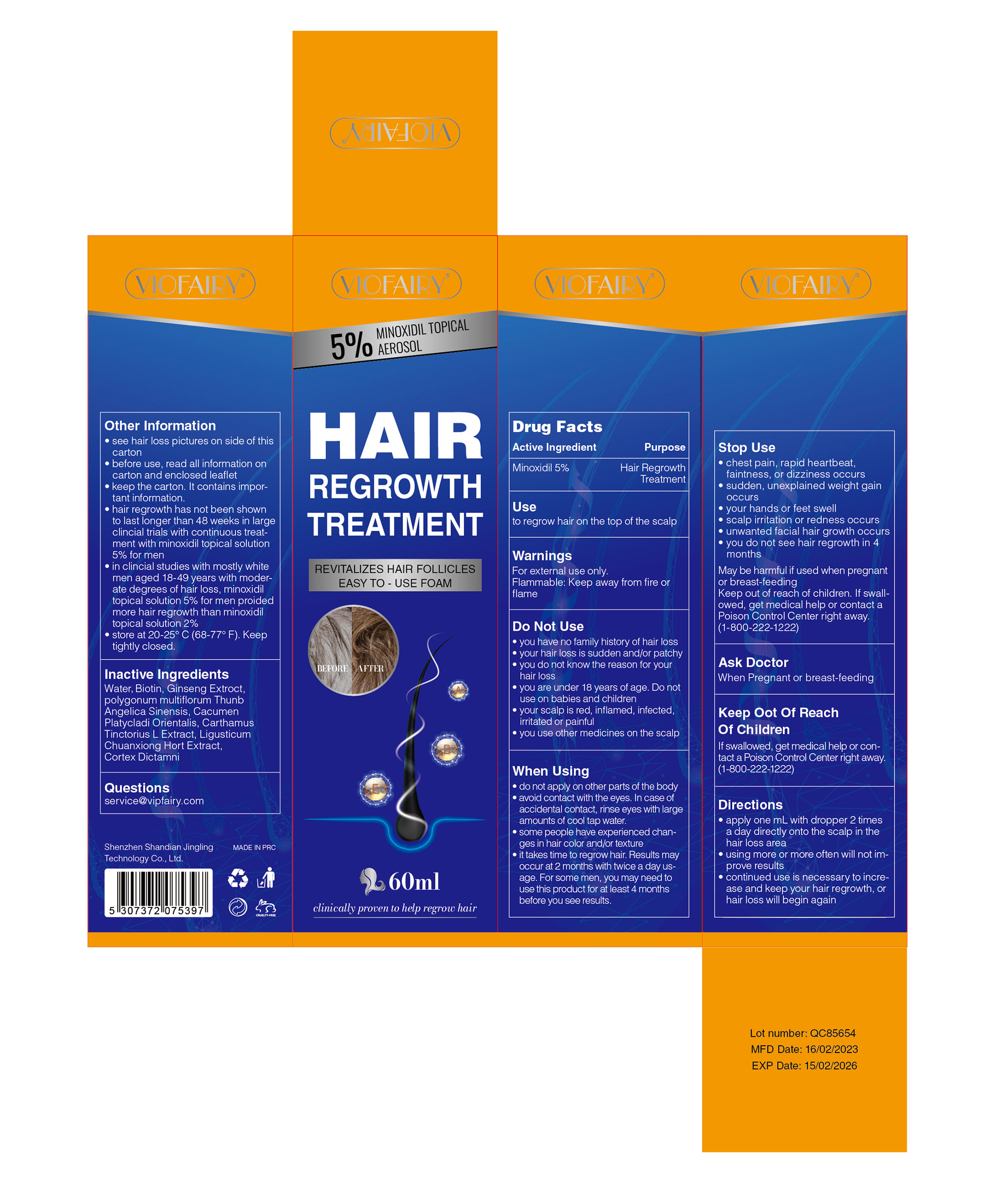 DRUG LABEL: HAIR GROWTH FOAM
NDC: 83804-008 | Form: AEROSOL, FOAM
Manufacturer: Shenzhen Shandian Jingling Technology Co., Ltd.
Category: otc | Type: HUMAN OTC DRUG LABEL
Date: 20250822

ACTIVE INGREDIENTS: MINOXIDIL 5 g/100 mL
INACTIVE INGREDIENTS: WATER; GLYCERIN; 1-BUTENE; NIACINAMIDE; REYNOUTRIA MULTIFLORA WHOLE; CAFFEINE; SODIUM COCOYL GLYCINATE; DIETHYL ETHANOLAMINE; PLATYCLADUS ORIENTALIS WHOLE; BISPHENOL A; BIOTIN; SODIUM HYALURONATE; HYDROXYACETOPHENONE; ZANTHOXYLUM BUNGEANUM FRUIT; LIGUSTRUM LUCIDUM FRUIT; GLYCOL; LIGUSTICUM WALLICHII ROOT; 3-O-ETHYL ASCORBIC ACID; PANTHENOL; ROSA CANINA FRUIT OIL

83804-008 HAIR GROWTH FOAM

ACTIVE INGREDIENT

MINOXIDIL 5%

PURPOSE

Hair Regrowth Treatment

INDICATIONS AND USAGE

to regrow hair on the top of the scalp

WARNINGS

For external use only.
Flammable: Keep away from fire or flame

DO NOT USE

you have no family history of hair loss
your hair loss is sudden and/or patchy
you do not know the reason for yourhair loss
you are under 18 years of age. Do notuse on babies and children
your scalp is red, inflamed, infectedirritated or painful
you use other medicines on the scalp

WHEN USING

do not apply on other parts of the body
avoid contact with the eyes. In case of accidental contact, rinse eyes with large amounts of cool tap water.
some people have experienced chan-ges in hair color and/or texture
it takes time to regrow hair. Results may occur at 2 months with twice a day us-age. For some men, you may need to use this product for at least 4 months before you see results

STOP USE

chest pain, rapid heartbeat.faintness, or dizziness occurs
sudden, unexplained weight gain occurs
your hands or feet swell
scalp irritation or redness occurs
unwanted facial hair growth occurs
you do not see hair regrowth in 4 months

KEEP OUT OF REACH OF CHILDREN

If swallowed,get medical help or con-tact a Poison Control Center right away.(1-800-222-1222)

DOSAGE AND ADMINISTRATION

apply one mL with dropper 2 times a day directly onto the scalp in the hair loss area
using more or more often will not im-prove results
continued use is necessary to incre-ase and keep your hair regrowth, or hair loss will begin again

INACTIVE INGREDIENT

water
minoxidil
glycerin
butylene
glycol
niacinamide
capilia longa biota orientalis leaf extract
polygonum multiflorumextract
ligustrum lucidum fruit
extractligusticum chuanxiong root
extract zanthoxylum bungeanum
fruit extract 3-o-ethylascorbic acid
rosa canina fruit oil
sodium cocoyl glycinate
biotin
panthenol
caffeine
sodium hyaluronate
diso-dium edta
hydroxyacetophenone
1.2-nexanedi0l